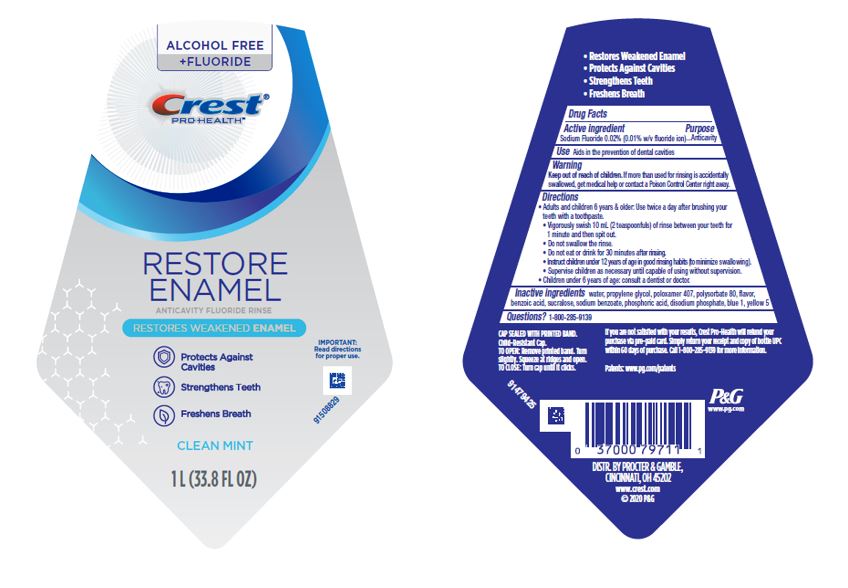 DRUG LABEL: Crest Pro-Health
NDC: 69423-909 | Form: RINSE
Manufacturer: The Procter & Gamble Manufacturing Company
Category: otc | Type: HUMAN OTC DRUG LABEL
Date: 20250806

ACTIVE INGREDIENTS: SODIUM FLUORIDE 0.2 mg/10 mL
INACTIVE INGREDIENTS: WATER; PROPYLENE GLYCOL; POLOXAMER 407; POLYSORBATE 80; BENZOIC ACID; PHOSPHORIC ACID; SUCRALOSE; SODIUM BENZOATE; SODIUM PHOSPHATE, DIBASIC, ANHYDROUS; FD&C YELLOW NO. 5; FD&C BLUE NO. 1

Crest Pro Health Restore Enamel

Drug Facts

Active ingredient

Sodium Fluoride 0.02% (0.01% w/v fluoride ion)

Purpose

Anticavity

Use

Aids in the prevention of dental cavities

Warnings

Keep out of reach of children. If more than used for rinsing is accidentally swallowed, get medical help or contact a Poison Control Center right away.

Directions

- Adults and children 6 years & older:
  Use twice a day after brushing your teeth with a toothpaste.
- Vigorously swish 10 mL (2 teaspoonfuls) of rinse between your teeth for 1 minute and then spit out.
- Do not swallow the rinse.
- Do not eat or drink for 30 minutes after rinsing.
- Instruct children under 12 years of age in good rinsing habits (to minimize swallowing).
- Supervise children as necessary until capable of using without supervision.
- Children under 6 years of age: Consult a dentist or doctor.

Inactive ingredients

water, propylene glycol, poloxamer 407, polysorbate 80, flavor, benzoic acid, sucralose, sodium benzoate, phosphoric acid, disodium phosphate, blue 1, yellow 5

Questions?

1–800–285–9139

DISTR. BY PROCTER & GAMBLE,

CINCINNATI, OH 45202

PRINCIPAL DISPLAY PANEL - 1000 mL Bottle Label

ALCOHOL FREE

+FLUORIDE

Crest ®

PRO-HEALTH™

ANTICAVITY FLUORIDE RINSE

RESTORES WEAKENED ENAMEL

IMPORTANT: Read directions for proper use.

Protects Against Cavities

Strengthens Teeth

Freshens Breath

CLEAN MINT

1L (33.8 FL OZ)